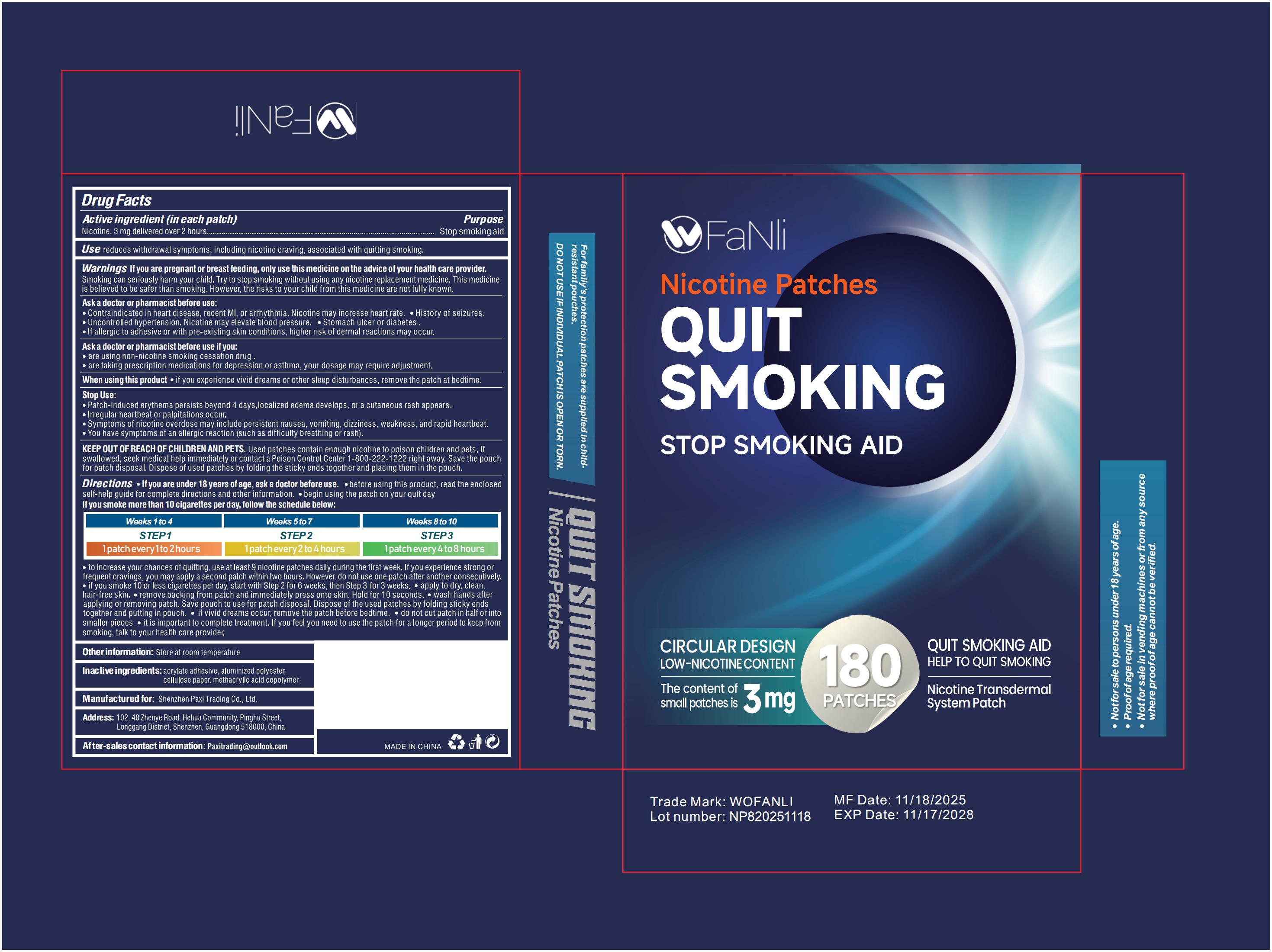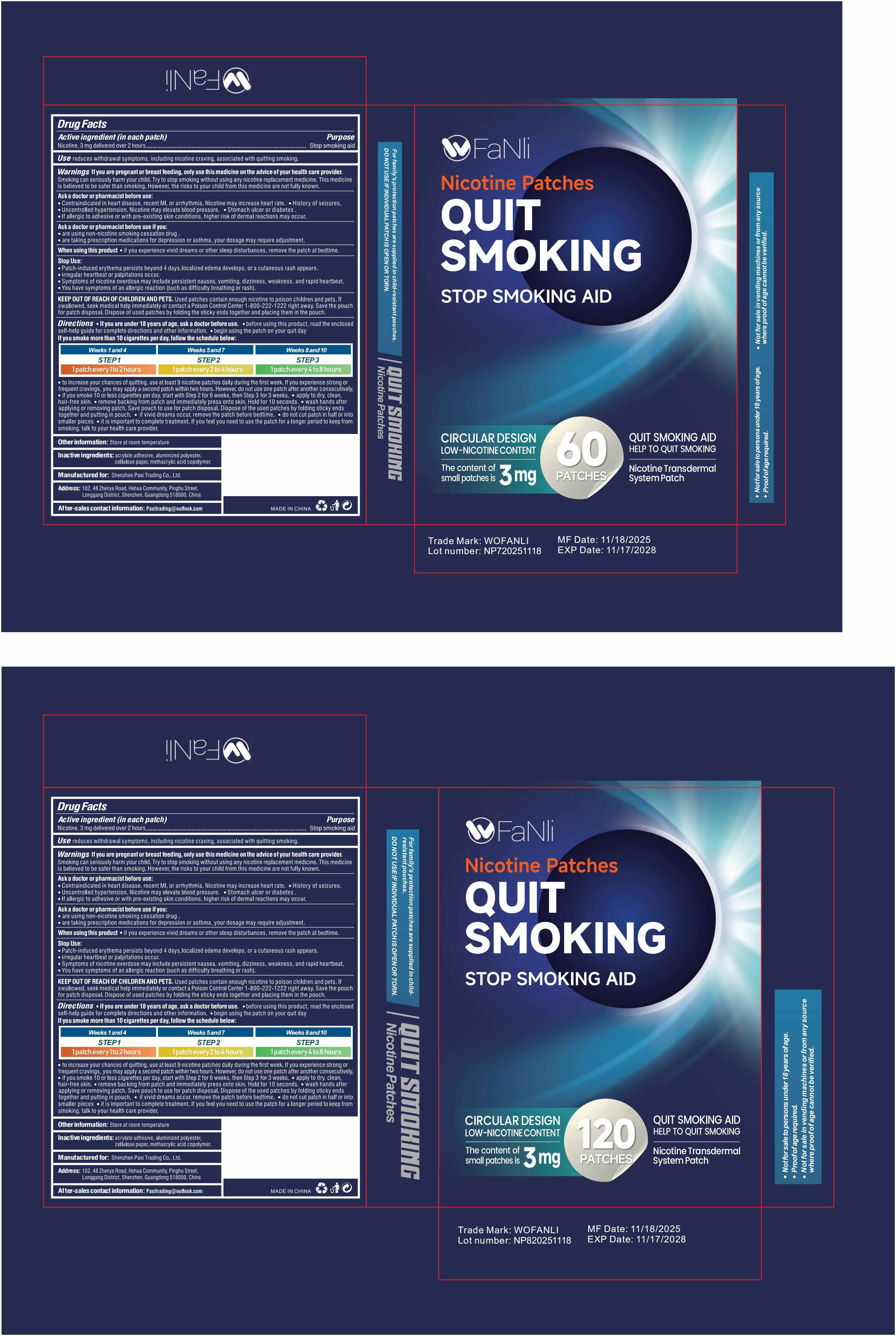 DRUG LABEL: WOFANLI Quit Smoking Nicotine Patches
NDC: 85835-016 | Form: PATCH
Manufacturer: Shenzhen Paxi Trading Co., Ltd.
Category: otc | Type: HUMAN OTC DRUG LABEL
Date: 20260105

ACTIVE INGREDIENTS: NICOTINE 3 mg/100 1
INACTIVE INGREDIENTS: ACRYLIC ACID; POWDERED CELLULOSE; POLYESTER-7; METHACRYLIC ACID - METHYL METHACRYLATE COPOLYMER (1:1)

85835-016 V2 add Pack 180Patchs

Active Ingredient

Nicotine 3mg

Purpose

Stop smoking aid

Use

Apply to dry, clean, hair-free skin.
Remove backing from patch and immediately press onto skin. Hold for 10 seconds.
Wash hands after applying or removing patch. Save pouch to use for patch disposal. Dispose of the used patches by folding sticky ends together and putting in pouch.
If vivid dreams occur, remove the patch before bedtime.
Do not cut patch in half or into smaller pieces
It is important to complete treatment. If you feel you need to use the patch for a longer period to keep from smoking, talk to your health care provider.

Warnings

If you are pregnant or breast feeding, only use this medicine on the advice of your health care provider.
Smoking can seriously harm your child. Try to stop smoking without using any nicotine replacement medicine. This medicine is believed to be safer than smoking. However, the risks to your child from this medicine are not fully known.

Do not use

Ask a doctor or pharmacist before use:
- Contraindicated in heart disease, recent MI, or arrhythmia. Nicotine may increase heart rate.
- History of seizures.
- Uncontrolled hypertension. Nicotine may elevate blood pressure.
- Stomach ulcer or diabetes .
- If allergic to adhesive or with pre-existing skin conditions, higher risk of dermal reactions may occur.

Ask Doctor

Ask a doctor or pharmacist before use if you:
- are using non-nicotine smoking cessation drug .
- are taking prescription medications for depression or asthma, your dosage may require adjustment.

When Using

When using this product
- if you experience vivid dreams or other sleep disturbances, remove the patch at bedtime.

Stop Use

- Patch-induced erythema persists beyond 4 days,localized edema develops, or a cutaneous rash appears.
- irregular heartbeat or palpitations occur.
- Symptoms of nicotine overdose may include persistent nausea, vomiting, dizziness, weakness, and rapid heartbeat.
- You have symptoms of an allergic reaction (such as difficulty breathing or rash).

KEEP OUT OF REACH OF CHILDREN AND PETS.
Used patches contain enough nicotine to poison children and pets. If swallowed, seek medical help immediately or contact a Poison Control Center 1-800-222-1222 right away. Save the pouch for patch disposal. Dispose of used patches by folding the sticky ends together and placing them in the pouch.

Directions

If you are under 18 years of age, ask a doctor before use.
before using this product, read the enclosed self-help guide for complete directions and other information
begin using the patch on your quit day
If you smoke more than 10 cigarettes per day, follow the schedule below:

Weeks 1 and 4
STEP 1
1 patch every 1 to 2 hours

Weeks 5 and 7
STEP 2
1 patch every 2 to 4 hours

Weeks 8 and 10
STEP 3
use I/2
patch/day

Weeks 9 and 10
STEP 3
1 patch every 4 to 8 hours

to increase your chances of quitting, use at least 9 nicotine patches daily during the first week. If you experience strong or frequent cravings, you may apply a second patch within two hours. However, do not use one patch after another consecutively.
if you smoke 10 or less cigarettes per day, start with Step 2 for 6 weeks, then Step 3 for 3 weeks.
Apply to dry, clean, hair-free skin.
Remove backing from patch and immediately press onto skin. Hold for 10 seconds.
Wash hands after applying or removing patch. Save pouch to use for patch disposal. Dispose of the used patches by folding sticky ends together and putting in pouch.
If vivid dreams occur, remove the patch before bedtime.
Do not cut patch in half or into smaller pieces
It is important to complete treatment. If you feel you need to use the patch for a longer period to keep from smoking, talk to your health care provider.

Other information

Store at room temperature

Inactive ingredients

acrylate adhesive, aluminized polyester,cellulose paper, methacrylic acid copolymer.

Questions

After-sales service contact information:
For any product inquiries, contact us: Paxitrading@outlook.com